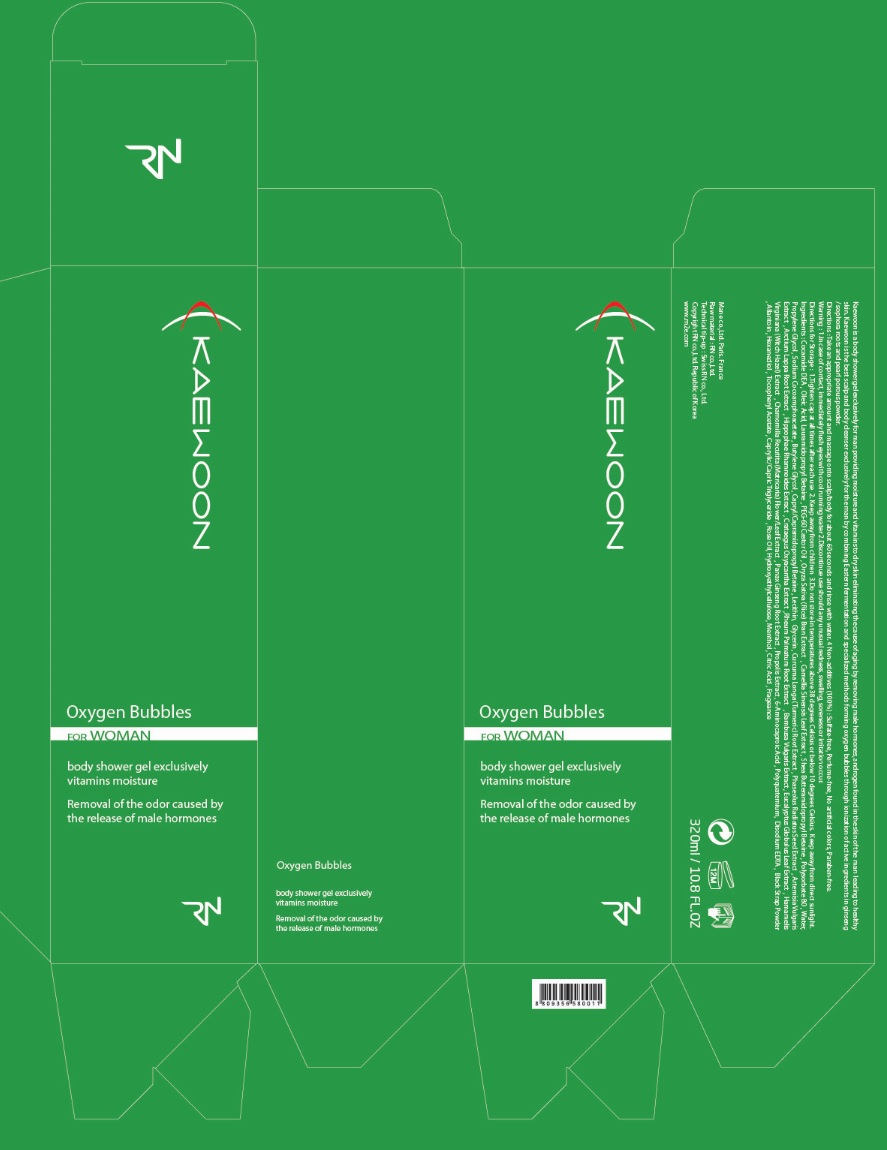 DRUG LABEL: KAEWOON FOR WOMEN
NDC: 71237-004 | Form: GEL
Manufacturer: RNCARE
Category: otc | Type: HUMAN OTC DRUG LABEL
Date: 20211004

ACTIVE INGREDIENTS: HYALURONIC ACID 20 mg/1 mL; ALLANTOIN 2 mg/1 mL
INACTIVE INGREDIENTS: WATER; SODIUM COCOATE; OLEIC ACID; COCO MONOISOPROPANOLAMIDE; DIGLYCERIN; BUTYLENE GLYCOL; POLYSORBATE 85; 1,2-HEXANEDIOL; SODIUM COCOAMPHOACETATE; RICE BRAN; GREEN TEA LEAF; TURMERIC; ARCTIUM LAPPA ROOT; HIPPOPHAE RHAMNOIDES SEED; RHEUM PALMATUM ROOT; BAMBUSA VULGARIS WHOLE; HAMAMELIS VIRGINIANA LEAF WATER; MATRICARIA CHAMOMILLA ROOT; SAPINDUS MUKOROSSI FRUIT; EDETATE DISODIUM ANHYDROUS; MENTHOL, UNSPECIFIED FORM

71237-004_V2

ACTIVE INGREDIENT

HYALURONIC ACID 2%

Allantoin 0.2%

PURPOSE

Skin Protectant

INDICATIONS AND USAGE

Body Cleansing

DOSAGE AND ADMINISTRATION

Take an appropriate amount and massage onto body for about 60 seconds and rinse with water

WARNINGS

In case of eye contact, immediately rinse with water

Stop use if unusual redness, swelling, soreness or irritation occur

Keep out of reach of children

INACTIVE INGREDIENT

Water, Sodium Cocoate, Oleic Acid, Cocamide MIPA, DiGlycerin, Butylene Glycol, Shea Butteramidopropyl Betaine, Hydrolyzed Collagen, Polysorbate85, 1,2-Hexanediol, Sodium Cocoamphoacetate, Oryza Sativa (Rice) Bran Extract, Camellia Sinensis Leaf Extract, Black Strap Powder, Curcuma Longa (Turmeric) Root Extract, Phaseolus Radiatus Seed Extract, Artemisia Vulgaris Extract, Arctium Lappa Root Extract, Hippophae Rhamnoides Extract, Crataegus Oxyacantha Extract, Rheum Palmatum Root Extract, Bambusa Vulgaris Extract, Eucalyptus Globulus Leaf Extract, Hamamelis Virginiana (Witch Hazel) Extract, Chamomilla Recutita (Matricaria) Flower/Leaf Extract, Sapindus Mukorossi Fruit Extract, Capryl/Capramidopropyl Betaine, Caprylic/Capric Triglycerid, Polyquaternium-10, Panax Ginseng Root Extract, Hydroxyethylcellulose, Disodium EDTA, Menthol, Mandelic Acid, Propolis Extract, Fragrance